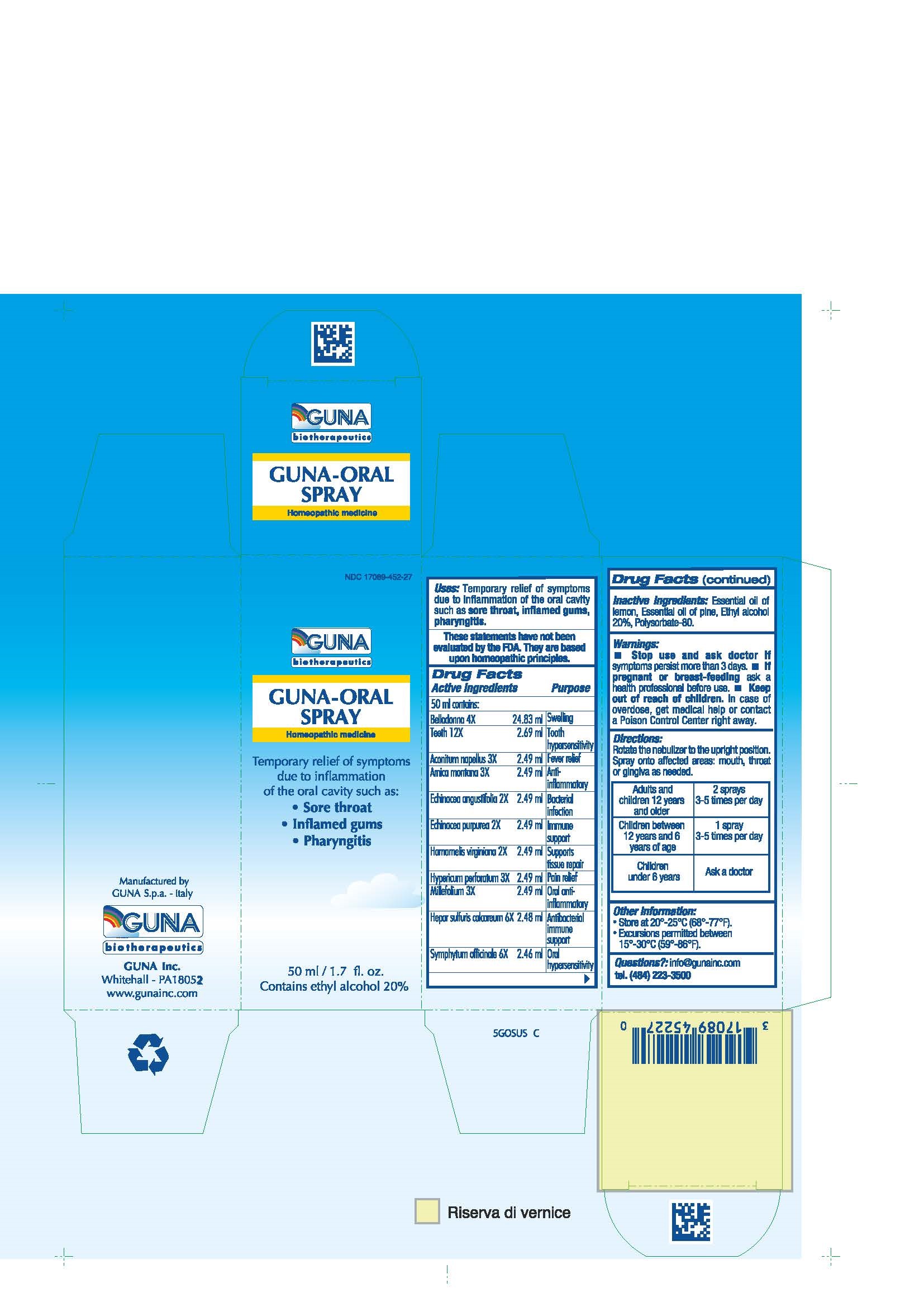 DRUG LABEL: GUNA-ORAL
NDC: 17089-452 | Form: SPRAY
Manufacturer: Guna spa
Category: homeopathic | Type: HUMAN OTC DRUG LABEL
Date: 20181221

ACTIVE INGREDIENTS: ACONITUM NAPELLUS 3 [hp_X]/30 mL; ARNICA MONTANA 3 [hp_X]/30 mL; ATROPA BELLADONNA 4 [hp_X]/30 mL; ECHINACEA ANGUSTIFOLIA 2 [hp_X]/30 mL; ECHINACEA PURPUREA 2 [hp_X]/30 mL; WITCH HAZEL 2 [hp_X]/30 mL; CALCIUM SULFIDE 6 [hp_X]/30 mL; HYPERICUM PERFORATUM 3 [hp_X]/30 mL; ACHILLEA MILLEFOLIUM 3 [hp_X]/30 mL; COMFREY ROOT 6 [hp_X]/30 mL; SUS SCROFA TOOTH 12 [hp_X]/30 mL
INACTIVE INGREDIENTS: ABIES SACHALINENSIS VAR. SACHALINENSIS OIL; ALCOHOL; LEMON OIL; POLYSORBATE 80

GUNA-ORAL SPRAY

ACTIVE INGREDIENTS/PURPOSE

ACONITUM NAPELLUS 3X ANTI-INFLAMMATORY
ARNICA MONTANA 3X FEVER RELIEF
BELLADONNA 4X SWELLING
ECHINACEA ANGUSTIFOLIA 2X BACTERIAL INFECTION
ECHINACEA PURPUREA 2X IMMUNE SUPPORT
HAMAMELIS VIRGINIANA 2X SUPPORTS TISSUE REPAIR
HEPAR SULFURIS CALCAREUM 6X ANTIBACTERIAL IMMUNE SUPPORT
HYPERICUM PERFORATUM 3X PAIN RELIEF
MILLEFOLIUM 3X ORAL ANTI- INFLAMMATORY
SYMPHYTUM OFFICINALE 6X ORAL HYPERSENSITIVITY
TEETH 12X TOOTH HYPERSENSITIVITY

USES

Temporary relief of symptoms due to inflammation of the oral cavity such as:

- Sore throat
- Inflamed gums
- Pharyngitis

WARNINGS

- Stop use and ask doctor if symptoms persist more than 3 days.
- If pregnant or breast-feeding ask a health professional before use.
- Keep out of reach of children. In case of overdose, get medical help or contact a Poison Control Center right away.
- Contains ethyl alcohol 20%

PREGNANCY

If pregnant or breast-feeding ask a doctor before use

WARNINGS

Keep out of reach of children

DIRECTIONS

Adults and children 12 years and older 2 sprays, 3-5 times per day
Children between 12 years and 6 years of age 1 spray t, 3-5 times per day
Children under 6 years ask a doctor

QUESTIONS

Questions?: info@gunainc.com
Tel. (484) 223-3500

INDICATIONS AND USAGE

Directions: Rotate the nebulizer to the upright position. Spray onto affected areas: mouth, throat or gingiva as needed.

INACTIVE INGREDIENT

Inactive ingredients: Essential oil of lemon, Essential oil of pine, Ethyl alcohol 20%, Polysorbate-80.